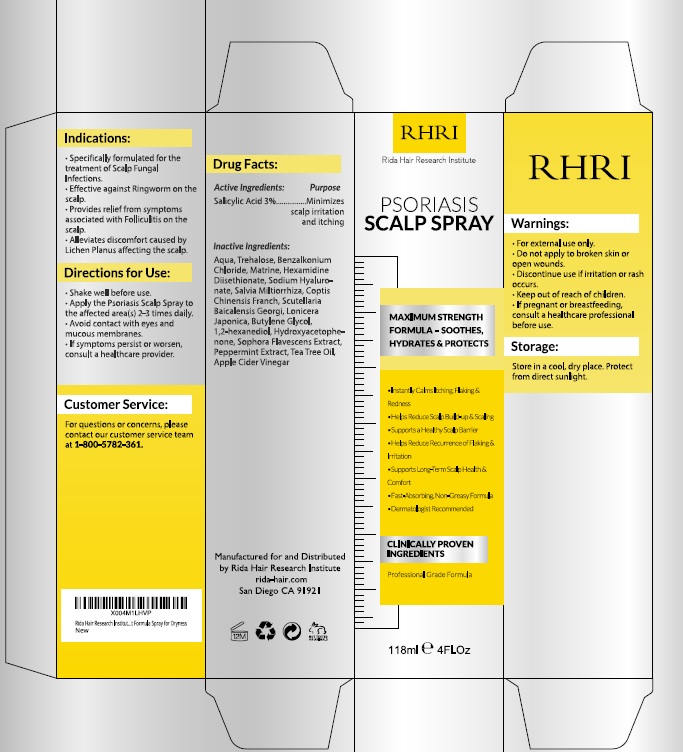 DRUG LABEL: Psoriasis Scalp Treatment
NDC: 83004-026 | Form: LIQUID
Manufacturer: Rida LLC
Category: otc | Type: HUMAN OTC DRUG LABEL
Date: 20250528

ACTIVE INGREDIENTS: SALICYLIC ACID 3 g/100 mL
INACTIVE INGREDIENTS: WATER; SODIUM C14-16 OLEFIN SULFONATE; COCAMIDOPROPYL BETAINE; PEG-120 METHYL GLUCOSE DIOLEATE; POLYQUATERNIUM-7; TROLAMINE; PANTHENOL; .ALPHA.-TOCOPHEROL ACETATE; TEA TREE OIL; GREEN TEA LEAF; ASCORBIC ACID

Active Ingredient

Salicylic Acid 3%

Purpose

Minimizes scalp irritation and itching

Uses

- Specifically formulated for the treatment of scalp fungal infections.
- Effective against ringworm on the scalp.
- Provides relief from symptoms associated with folliculitis on the scalp.
- Alleviates discomfort caused by lichen planus affecting the scalp.

Warnings

- For external use only.
- Do not apply to broken skin or open wounds.
- Discontinue use if irritation or rash occurs.
- Keep out of reach of children.
- If pregnant or breastfeeding, consult a healthcare professional before use.

Directions

- Shake well before use.
- Apply the Folliculitis Scalp Spray to the affected area 2–3 times daily.
- Avoid contact with eyes and mucous membranes.
- If symptoms persist or worsen, consult a healthcare provider.

Other Information

- Store in a cool, dry place. Protect from direct sunlight.

Inactive ingredients

Aqua (Water), Trehalose, Benzalkonium Chloride, Mirtazapine, Hexamidine, Sodium Hyaluronate, Salvia Miltiorrhiza Extract, Ginkgo Biloba Extract, Bacillus Subtilis Ferment, Coptis Chinensis Extract, 1,2-Hexanediol, Hydroxypropyl Guar, Saponins, Apple Cider Vinegar